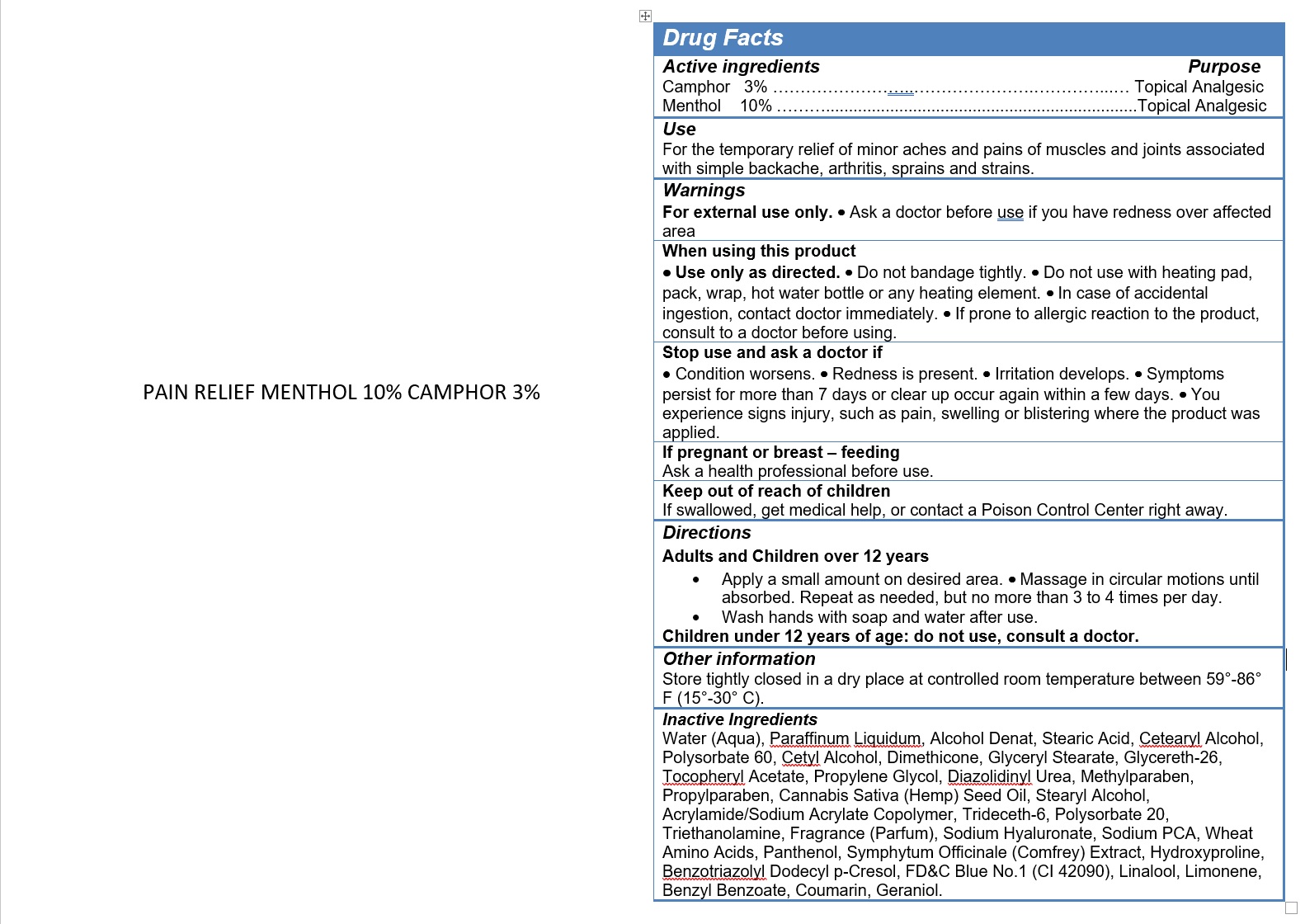 DRUG LABEL: MENTHOL, CAMPHOR
NDC: 49283-582 | Form: CREAM
Manufacturer: CHEMCO CORPORATION
Category: otc | Type: HUMAN OTC DRUG LABEL
Date: 20260218

ACTIVE INGREDIENTS: CAMPHOR (NATURAL) 3 g/100 g; MENTHOL, UNSPECIFIED FORM 10 g/100 g
INACTIVE INGREDIENTS: PANTHENOL; ALCOHOL; POLYSORBATE 60; CETYL ALCOHOL; DIMETHICONE 1000; .ALPHA.-TOCOPHEROL ACETATE; LINALOOL, (+/-)-; TRIDECETH-6; AMINO ACIDS, WHEAT; BENZYL BENZOATE; HYDROXYPROLINE; GLYCERYL MONOSTEARATE; GLYCERETH-26; STEARYL ALCOHOL; TRIBUTYL CITRATE; GERANIOL; DIAZOLIDINYL UREA; TROLAMINE; BUTETH-3; SODIUM BENZOTRIAZOLYL BUTYLPHENOL SULFONATE; CETOSTEARYL ALCOHOL; POLYSORBATE 20; HYALURONATE SODIUM; LIMONENE, (+)-; FD&C BLUE NO. 1; COUMARIN; METHYLPARABEN; SODIUM PYRROLIDONE CARBOXYLATE; PROPYLENE GLYCOL; PROPYLPARABEN; CANNABIS SATIVA SEED OIL; SYMPHYTUM OFFICINALE WHOLE; STEARIC ACID; WATER; MINERAL OIL

49283-582-16

ACTIVE INGREDIENT

Camphor 3%

Menthol 10%

PURPOSE

Topical Analgesic

USE

For the temporary relief of minor aches and pains of muscles and joints associated with simple backache, arthritis, sprains and strains.

WARNINGS

For external use only. · Ask a doctor before use if you have redness over affected area

WHEN USING

Use only as directed.
Do not bandage tightly.
Do not use with heating pad, pack, wrap, hot water bottle or any heating element.
In case of accidental ingestion, contact doctor immediately.

If prone to allergic reaction to the product, consult to a doctor before using.

STOP USE

Condition worsens.
Redness is present.
Irritation develops.
Symptoms persist for more than 7 days or clear up occur again within a few days.

You experience signs injury, such as pain, swelling or blistering where the product was applied.

If pregnant or breast – feeding

Ask a health professional before use.

KEEP OUT OF REACH OF CHILDREN

If swallowed, get medical help, or contact a Poison Control Center right away.

Directions

Adults and Children over 12 years

Apply a thin layer to the affected area and rub gently not more than 3 to 4 times a day.
Wash hands with soap and water after use.

Children under 12 years of age: do not use, consult a doctor.

OTHER SAFETY INFORMATION

Store tightly closed in a dry place at controlled room temperature between 59°-86° F (15°-30° C).

INACTIVE INGREDIENT

Water (Aqua), Paraffinum Liquidum, Alcohol Denat, Stearic Acid, Cetearyl Alcohol, Polysorbate 60, Cetyl
Alcohol, Dimethicone, Glyceryl Stearate, Glycereth-26, Tocopheryl Acetate, Propylene Glycol, Diazolidinyl
Urea, Methylparaben, Propylparaben, Cannabis Sativa Seed Oil, Stearyl Alcohol, Acrylamide/Sodium
Acrylate Copolymer, Trideceth-6, Polysorbate 20, Triethanolamine, Fragrance (Parfum), Sodium
Hyaluronate, Sodium PCA, Wheat Amino Acids, Panthenol, Symphytum Officinale (Comfrey) Extract,
Hydroxyproline, Sodium Benzotriazolyl Butylphenol Sulfonate, Buteth-3, Tributyl Citrate,
FD&C Blue No.1 (CI 42090), Linalool, Limonene, Benzyl Benzoate, Coumarin, Geraniol.